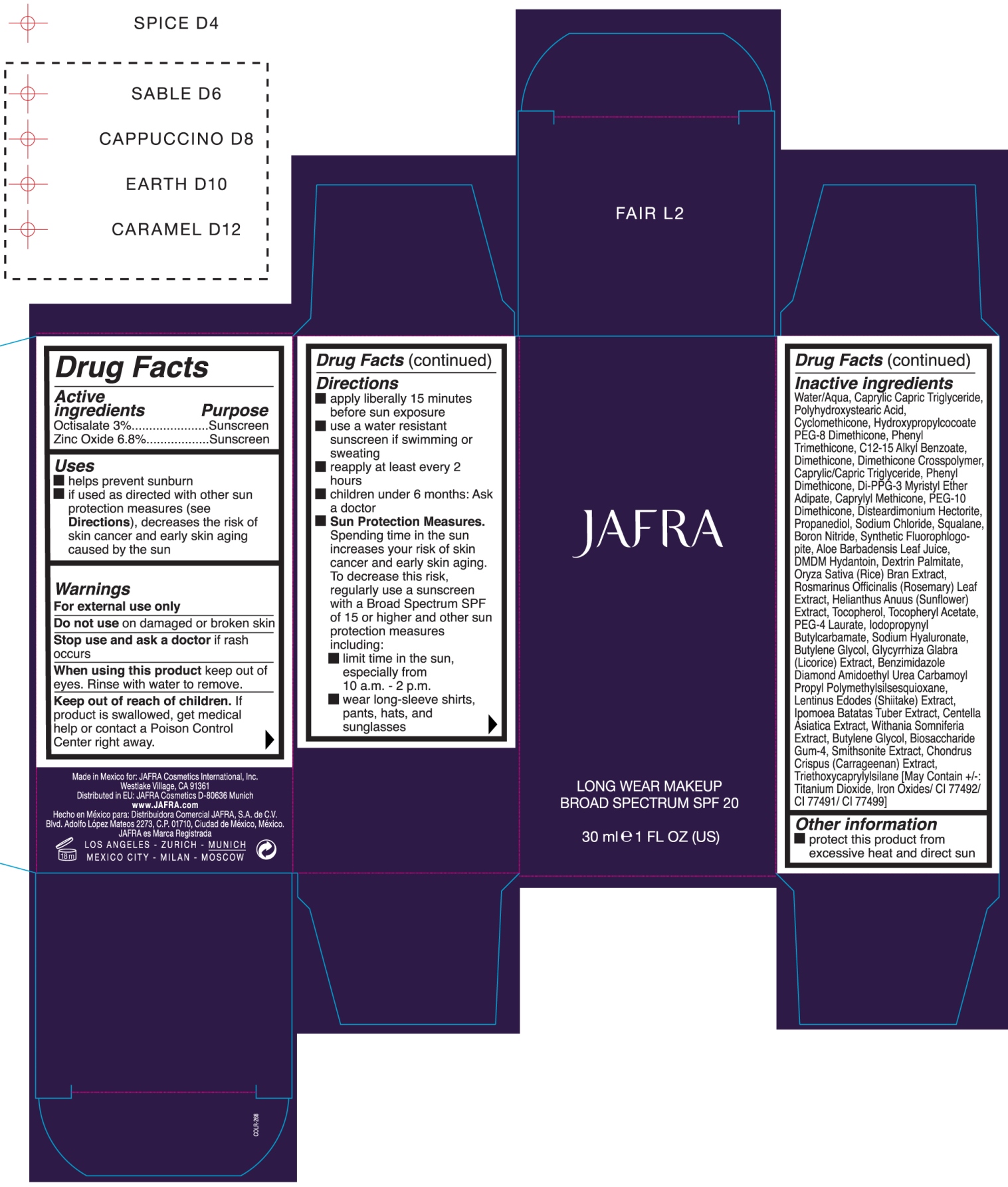 DRUG LABEL: Long Wear Makeup Broad Spectrum SPF 20 Nude
NDC: 68828-263 | Form: CREAM
Manufacturer: JAFRA COSMETICS INTERNATIONAL
Category: otc | Type: HUMAN OTC DRUG LABEL
Date: 20200623

ACTIVE INGREDIENTS: OCTISALATE 3 g/100 mL; ZINC OXIDE 6.8 g/100 mL
INACTIVE INGREDIENTS: WATER; MEDIUM-CHAIN TRIGLYCERIDES; POLYHYDROXYSTEARIC ACID (2300 MW); CYCLOMETHICONE; HYDROXYPROPYLCOCOATE PEG-8 DIMETHICONE; PHENYL TRIMETHICONE; ALKYL (C12-15) BENZOATE; DIMETHICONE; DIMETHICONE CROSSPOLYMER (450000 MPA.S AT 12% IN CYCLOPENTASILOXANE); DI-PPG-3 MYRISTYL ETHER ADIPATE; CAPRYLYL TRISILOXANE; PEG-10 DIMETHICONE (600 CST); DISTEARDIMONIUM HECTORITE; PROPANEDIOL; SODIUM CHLORIDE; SQUALANE; BORON NITRIDE; ALOE VERA LEAF; DMDM HYDANTOIN; DEXTRIN PALMITATE (CORN; 20000 MW); RICE BRAN; ROSEMARY; HELIANTHUS ANNUUS FLOWERING TOP; TOCOPHEROL; .ALPHA.-TOCOPHEROL ACETATE; PEG-4 LAURATE; IODOPROPYNYL BUTYLCARBAMATE; HYALURONATE SODIUM; BUTYLENE GLYCOL; LICORICE; LENTINULA EDODES MYCELIUM; SWEET POTATO; CENTELLA ASIATICA; WITHANIA SOMNIFERA LEAF; BIOSACCHARIDE GUM-4; CHONDRUS CRISPUS CARRAGEENAN; TRIETHOXYCAPRYLYLSILANE

Long Wear Makeup Broad Spectrum SPF 20 Nude

Active

Ingredients Purpose

Octisalate 3% ...... Sunscreen

Zinc Oxide 6.8% .... Sunscreen

Uses

- helps prevent suburn
- if used as directed with other sun protection measures (see Directions), decreases the risk of skin cancer and early skin aging caused by the sun

Keep out of reach of children. If product is swallowed, get medical help or contact a Poison Control Center right away.

Stop use and ask a doctor if rash occurs

Warnings

- For external use only
- Do not use on damaged or broken skin
- When using this product keep out of eyes. Rinse with water to remove.

Directions

- apply liberally 15 minutes before sun exposure
- use a water resistant sunscreen if swimming or sweating
- reapply at least every 2 hours
- children under 6 months: Ask a doctor
- Sun Protection Measures. Spending time in the sun increases your risk of skin cancer and early skin aging. To decrease this risk, regularly use a sunscreen with a Broad Spectrum SPF of 15 or higher and other sun protection measures including:
- limit time in the sun, especially from 10 a.m. - 2 p.m.
- wear long-sleeve shirts, pants, hats, and sunglasses

INACTIVE INGREDIENT

Water/Aqua, Caprylic Capric Triglyceride, Polyhydroxystearic Acid, Cyclomethicone, Hydroxypropylcocoate PEG-8 Dimethicone, Phenyl Triemthicone, C12-15 Alkyl Benzoate, Dimethicone, Dimethicone Crosspolymer, Caprylic/Capric Triglyceride, Phenyl Dimethicone, Di-PPG-3 Myristyl Ether Adipate, Caprylyl Methicone, PEG-10 Dimethicone, Disteardimonium Hectorite, Propanediol, Sodium Chloride, Squalane,Boron Nitride, Synthetic Fluorophlogopite, Aloe Barbadensis Leaf Juice, DMDM Hydantoin, Dextrin Palmitate, Oryza Sativa (Rice) Bran Extract, Rosmarinus Officinalis (Rosemary) Leaf Extract, Helianthus Anuus (Sunflower) Extract, Tocopherol, Tocopheryl Acetate, PEG-4 Laurate, Iodopropynyl Butylcarbamate, Sodium Hyaluronate, Butylene Glycol, Glycyrrhiza Glabra (Licorice) Extract, Benzimidazole Diamond Amidoethyl Urea Carbamoyl Propyl Polymehtylsilsesquioxane, Lentinus Edodes (shiitake) Extract, Ipomoea Batatas Tuber Extract, Centella Asiatica Extract, Withania Somniferia Extract, Butylene Glycol, Biosaccharide Gum-4, Smithsonite Extact, Chondrus Crispus (Carrageenan) Extract, Triethoxycaprylylsilane [May Containt +/-: Titanium Dioxide, Iron Oxides/ CI 77492/ CI 77491/ CI 77499]

PACKAGE LABEL

JAFRA

Long Wear Makeup

Broad Spectrum SPF 20

30 ml / 1 FL oz (us)